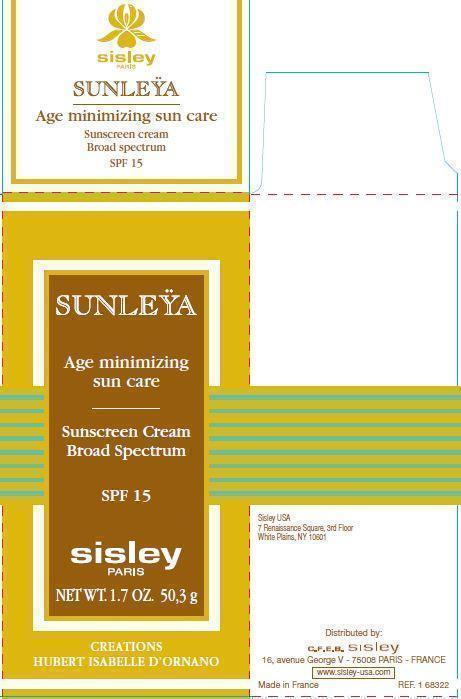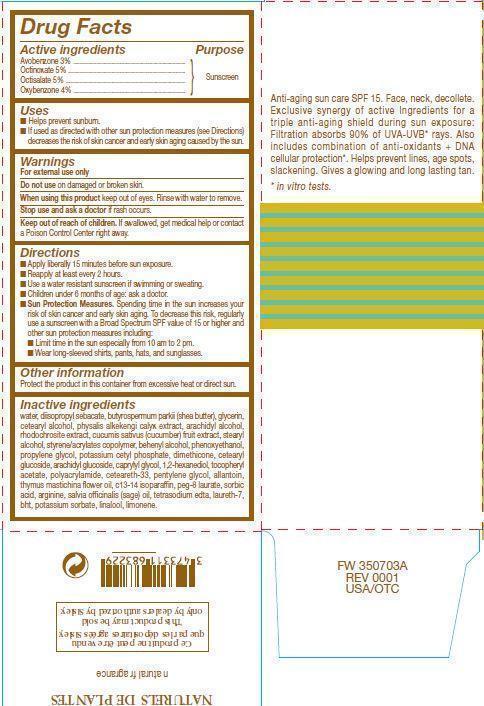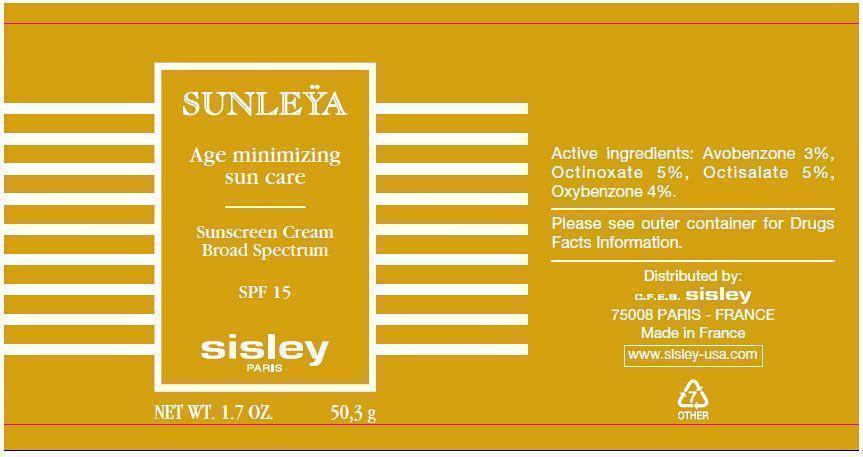 DRUG LABEL: 
                  SUNLEYA Age minimizing sun care

                
                  

NDC: 66097-002 | Form: CREAM
Manufacturer: C.F.E.B. Sisley
Category: otc | Type: HUMAN OTC DRUG LABEL
Date: 20241210

ACTIVE INGREDIENTS: AVOBENZONE 30 mg/1 g; OCTINOXATE 50 mg/1 g; OCTISALATE 50 mg/1 g; OXYBENZONE 40 mg/1 g
INACTIVE INGREDIENTS: WATER; DIISOPROPYL SEBACATE; SHEANUT OIL; GLYCERIN; CETOSTEARYL ALCOHOL; PHYSALIS ALKEKENGI CALYX; ARACHIDYL ALCOHOL; MANGANESE CARBONATE; CUCUMBER; STEARYL ALCOHOL; DOCOSANOL; PHENOXYETHANOL; PROPYLENE GLYCOL; POTASSIUM CETYL PHOSPHATE; DIMETHICONE; CETEARYL GLUCOSIDE; ARACHIDYL GLUCOSIDE; CAPRYLYL GLYCOL; 1,2-HEXANEDIOL; .ALPHA.-TOCOPHEROL ACETATE; CETEARETH-33; PENTYLENE GLYCOL; ALLANTOIN; THYMUS MASTICHINA FLOWERING TOP OIL; C13-14 ISOPARAFFIN; PEG-8 LAURATE; SORBIC ACID; ARGININE; SAGE OIL; EDETATE SODIUM; LAURETH-7; BUTYLATED HYDROXYTOLUENE; POTASSIUM SORBATE; LINALOOL, (+/-)-

SUNLEYA Age minimizing sun care SPF 15

Active ingredients

Avobenzone 3 % Octinoxate 5 % Octisalate 5 % Oxybenzone 4 %

Purpose

Sunscreen

Uses

- Helps prevent sunburn
- If used as directed with other sun protection measures (see Directions) decreases the risk of skin cancer and early skin aging caused by the sun.

Warnings

For external use only

Do not use

on damaged or broken skin.

When using this product

keep out of eyes. Rinse with water to remove.

Stop use and ask a doctor

if rash occurs.

Keep out of reach of children.

If swallowed, get medical help or contact a Poison Control Center right away.

Directions

- Apply liberally 15 minutes before sun exposure.
- Reapply at least every 2 hours.
- Use a water resistant sunscreen if swimming or sweating.
- Children under 6 months of age: ask a doctor.
- Spending time in the sun increases your risk of skin cancer and early skin aging. To decrease this risk, regularly use a sunscreen with a Broad Spectrum SPF value of 15 or higher and other sun protection measures including: Sun Protection Measures:
- Limit time in the sun especially from 10 am to 2 pm.
- Wear long-sleeved shirts, pants, hats, and sunglasses.

Other information

Protect the product in this container from excessive heat or direct sun.

Inactive ingredients

water, diisopropyl sebacate, butyrospermum parkii (shea butter), glycerin, cetearyl alcohol, physalis alkekengi calyx extract, arachidyl alcohol, rhodochrosite extract, cucumis sativus (cucumber) fruit extract, stearyl alcohol, styrene/acrylates copolymer, behenyl alcohol, phenoxyethanol, propylene glycol, dimethicone, cetearyl glucoside, arachidyl glucoside, caprylyl glycol, 1,2-hexanediol, tocopheryl acetate, polyacrylamide, ceteareth-33, pentylene glycol, allantoin, thymus mastichina flower oil, c13-14 isoparaffin, peg-8 laurate, sorbic acid, arginine, salvia officinalis (sage) oil, laureth-7, bht, potassium sorbate, linalool, limonene

PACKAGE LABEL

SUNLEYA Age minimizing sun care Sunscreen Cream Broad Spectrum SPF 15 sisley PARIS NET WT. 1.7 OZ. 50,3 g CREATIONS HUBERT ISABELLE D'ORNANO Sisley USA 7 Renaissance Square, 3rd Floor, White Plains, NY 10601 Anti-aging sun care SPF 15. Face, neck decollete. Exclusive synergy of active ingredients for a triple anti-aging shield during sun exposure: Filtration absorbs 90% of UVA-UVB* rays. Also includes combination of anti-oxidants + DNA cellular protection*. Helps prevent lines, age spots, slackening. Gives a growing and long lasting tan. *
in vitro tests